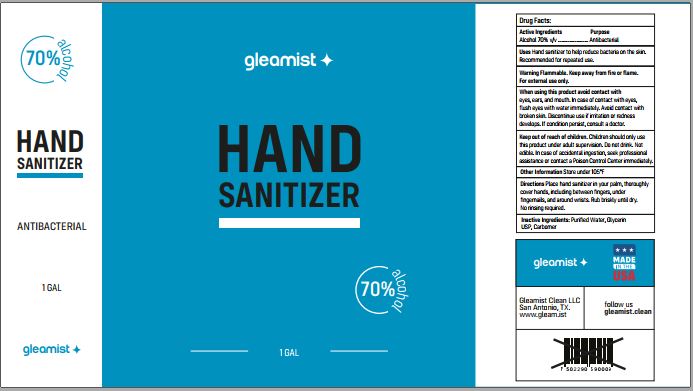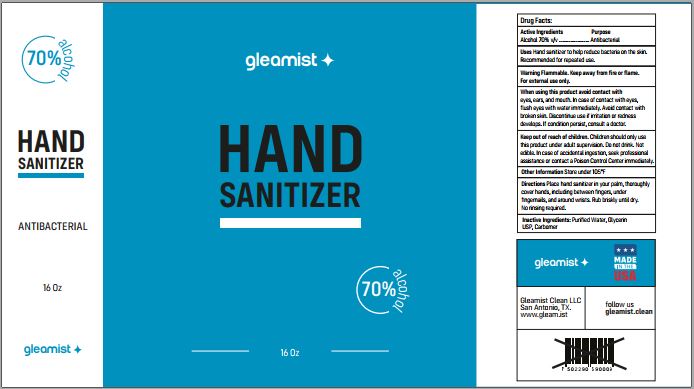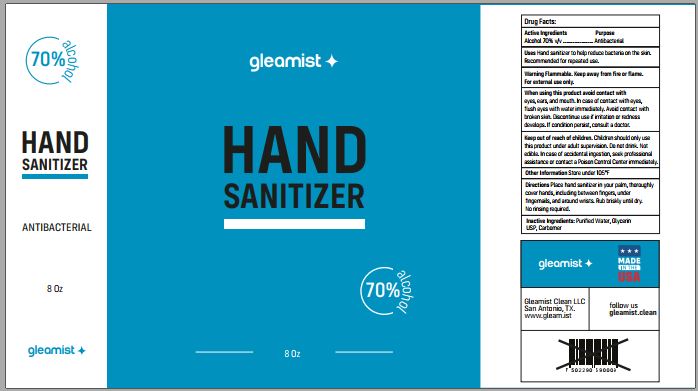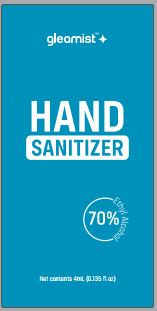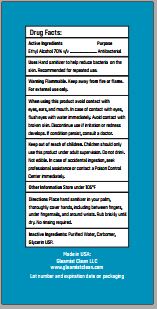 DRUG LABEL: Gleamist Hand Sanitizer
NDC: 78174-053 | Form: GEL
Manufacturer: Custom Chemical Services, LLC
Category: otc | Type: HUMAN OTC DRUG LABEL
Date: 20210427

ACTIVE INGREDIENTS: ALCOHOL 70.0882 L/100 L
INACTIVE INGREDIENTS: GLYCERIN 0.0678 L/100 L; water 29.4866 L/100 L; AMMONIUM POLYACRYLOYLDIMETHYL TAURATE (55000 MPA.S) 0.3574 1/100 L

Active Ingredients

Alcohol 70% v/v

Purpose

Antibacterial

INDICATIONS AND USAGE

Uses Hand sanitizer to help reduce bacteria on the skin. Recommended for repeated use.

WARNINGS

Warning Flammable. Keep away from fire or flame. For external use only.

WHEN USING

When using this productavoid contact with eyes, ears, and mouth. In case of contact with eyes, flush eyes with water immediately. Avoid contact with broken skin. Discontinue use if irritation or redness develops. If condition persists, consult a doctor.

Keep out of reach of children. Children should only use this product under adult supervison. Do not drink. Not edible. In case of accidential ingestion, seek professional assistance or contact a Poison Control Center immediately.

Other Information Store under 105°F.

DOSAGE AND ADMINISTRATION

Directions Place hand sanitizer in your palm, thoroughly cover hands, including between fingers, under fingernails, and around wrists. Rub briskly until dry. No rinsing required.

Inactive Ingredients Purified water, Glycerin USP, Carbomer

PACKAGE LABEL

01 – 1 Gallon:

03 – 16 oz:

05 – 8 oz:

10 – 4 mL: